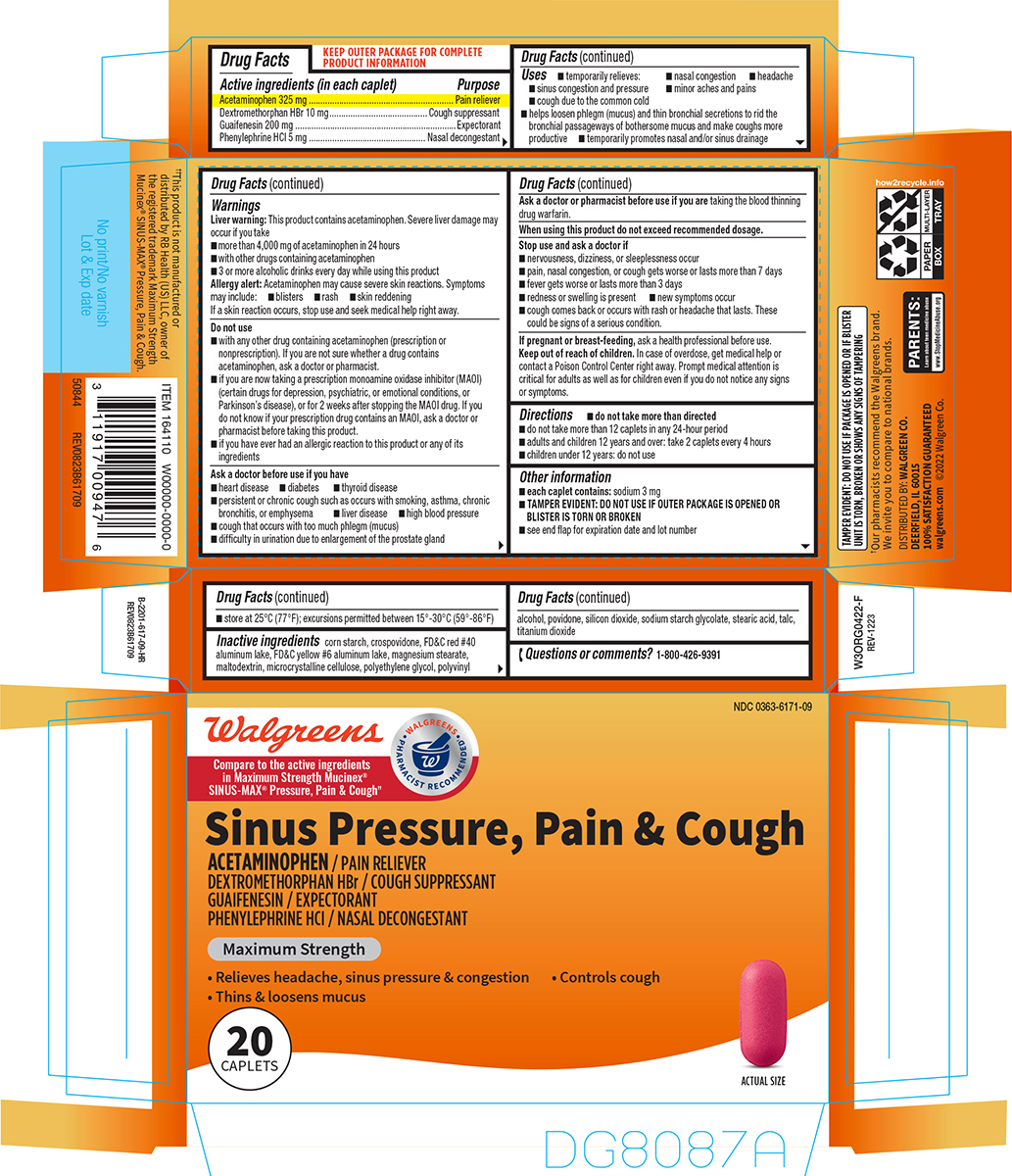 DRUG LABEL: Sinus Pressure, Pain and Cough
NDC: 0363-6171 | Form: TABLET, FILM COATED
Manufacturer: Walgreen Company
Category: otc | Type: HUMAN OTC DRUG LABEL
Date: 20260225

ACTIVE INGREDIENTS: ACETAMINOPHEN 325 mg/1 1; DEXTROMETHORPHAN HYDROBROMIDE 10 mg/1 1; GUAIFENESIN 200 mg/1 1; PHENYLEPHRINE HYDROCHLORIDE 5 mg/1 1
INACTIVE INGREDIENTS: STARCH, CORN; CROSPOVIDONE, UNSPECIFIED; FD&C RED NO. 40 ALUMINUM LAKE; FD&C YELLOW NO. 6 ALUMINUM LAKE; MAGNESIUM STEARATE; MALTODEXTRIN; MICROCRYSTALLINE CELLULOSE; POLYETHYLENE GLYCOL, UNSPECIFIED; POLYVINYL ALCOHOL, UNSPECIFIED; POVIDONE, UNSPECIFIED; SILICON DIOXIDE; SODIUM STARCH GLYCOLATE TYPE A POTATO; STEARIC ACID; TALC; TITANIUM DIOXIDE

Walgreens 44-617

Active ingredients (in each caplet)

Acetaminophen 325 mg
Dextromethorphan HBr 10 mg
Guaifenesin 200 mg
Phenylephrine HCl 5 mg

Purpose

Pain reliever
Cough suppressant
Expectorant
Nasal decongestant

Uses

- temporarily relieves:
  - nasal congestion
  - headache
  - sinus congestion and pressure
  - minor aches and pains
  - cough due to the common cold
- helps loosen phlegm (mucus) and thin bronchial secretions to rid the bronchial passageways of bothersome mucus and make coughs more productive
- temporarily promotes nasal and/or sinus drainage

Warnings

Liver warning: This product contains acetaminophen. Severe liver damage may occur if you take

- more than 4,000 mg of acetaminophen in 24 hours
- with other drugs containing acetaminophen
- 3 or more alcoholic drinks every day while using this product

Allergy alert: Acetaminophen may cause severe skin reactions. Symptoms may include:

- blisters
- rash
- skin reddening

If a skin reaction occurs, stop use and seek medical help right away.

Do not use

- with any other drug containing acetaminophen (prescription or nonprescription). If you are not sure whether a drug contains acetaminophen, ask a doctor or pharmacist.
- if you are now taking a prescription monoamine oxidase inhibitor (MAOI) (certain drugs for depression, psychiatric, or emotional conditions, or Parkinson’s disease), or for 2 weeks after stopping the MAOI drug. If you do not know if your prescription drug contains an MAOI, ask a doctor or pharmacist before taking this product.
- if you have ever had an allergic reaction to this product or any of its ingredients

Ask a doctor before use if you have

- heart disease
- diabetes
- thyroid disease
- persistent or chronic cough such as occurs with smoking, asthma, chronic bronchitis, or emphysema
- liver disease
- high blood pressure
- cough that occurs with too much phlegm (mucus)
- difficulty in urination due to enlargement of the prostate gland

Ask a doctor or pharmacist before use if you are

taking the blood thinning drug warfarin.

When using this product

do not exceed recommended dosage.

Stop use and ask a doctor if

- nervousness, dizziness, or sleeplessness occur
- pain, nasal congestion, or cough gets worse or lasts more than 7 days
- fever gets worse or lasts more than 3 days
- redness or swelling is present
- new symptoms occur
- cough comes back or occurs with rash or headache that lasts. These could be signs of a serious condition.

If pregnant or breast-feeding,

ask a health professional before use.

Keep out of reach of children.

In case of overdose, get medical help or contact a Poison Control Center right away. Prompt medical attention is critical for adults as well as for children even if you do not notice any signs or symptoms.

Directions

- do not take more than directed
- do not take more than 12 caplets in any 24-hour period
- adults and children 12 years and over: take 2 caplets every 4 hours
- children under 12 years: do not use

Other information

- each caplet contains: sodium 3 mg
- TAMPER EVIDENT: DO NOT USE IF OUTER PACKAGE IS OPENED OR BLISTER IS TORN OR BROKEN
- see end flap for expiration date and lot number
- store at 25°C (77°F); excursions permitted between 15°-30°C (59°-86°F)

Inactive ingredients

corn starch, crospovidone, FD&C red #40 aluminum lake, FD&C yellow #6 aluminum lake, magnesium stearate, maltodextrin, microcrystalline cellulose, polyethylene glycol, polyvinyl alcohol, povidone, silicon dioxide, sodium starch glycolate, stearic acid, talc, titanium dioxide

Questions or comments?

1-800-426-9391

Principal display panel

NDC 0363-6171-09

Walgreens
WALGREENS PHARMACIST RECOMMENDED†

Compare to the active ingredients
in Maximum Strength Mucinex®
SINUS-MAX® Pressure, Pain & Cough††

Sinus Pressure, Pain & Cough

ACETAMINOPHEN / PAIN RELIEVER
DEXTROMETHORPHAN HBr / COUGH SUPPRESSANT
GUAIFENESIN / EXPECTORANT
PHENYLEPHRINE HCl / NASAL DECONGESTANT

Maximum Strength

• Relieves headache, sinus pressure & congestion • Controls cough
• Thins & loosens mucus

20
CAPLETS

ACTUAL SIZE

TAMPER EVIDENT: DO NOT USE IF PACKAGE IS OPENED OR IF BLISTER
UNIT IS TORN, BROKEN OR SHOWS ANY SIGNS OF TAMPERING

†Our pharmacists recommend the Walgreens brand.
We invite you to compare to national brands.

DISTRIBUTED BY: WALGREEN CO.
DEERFIELD, IL 60015
100% SATISFACTION GUARANTEED
walgreens.com ©2022 Walgreen Co.

PARENTS:
Learn about teen medicine abuse
www.StopMedicineAbuse.org

††This product is not manufactured or
distributed by RB Health (US) LLC, owner of
the registered trademark Maximum Strength
Mucinex® SINUS-MAX® Pressure, Pain & Cough.

50844 REV0823B61709

Walgreens 44-617